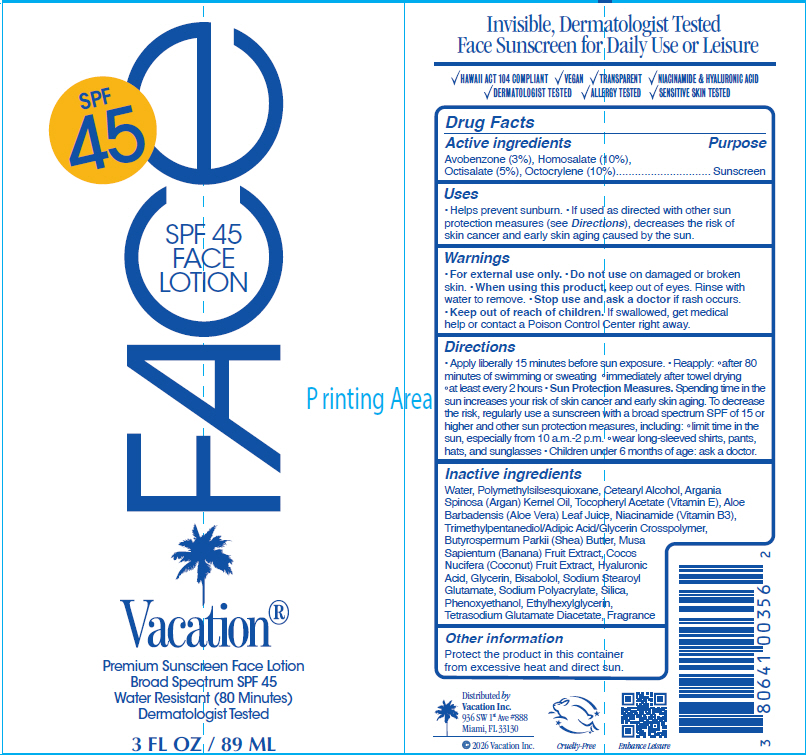 DRUG LABEL: Vacation Face
NDC: 80641-031 | Form: LOTION
Manufacturer: Vacation INC.
Category: otc | Type: HUMAN OTC DRUG LABEL
Date: 20251229

ACTIVE INGREDIENTS: Avobenzone 3 g/100 mL; Homosalate 10 g/100 mL; Octisalate 5 g/100 mL; Octocrylene 10 g/100 mL
INACTIVE INGREDIENTS: Water; Cetostearyl Alcohol; Polymethylsilsesquioxane (11 Microns); Argan Oil; Aloe Vera Leaf; Niacinamide; Phenoxyethanol; .Alpha.-Tocopherol Acetate; Sodium Stearoyl Glutamate; Trimethylpentanediol/Adipic Acid/Glycerin Crosspolymer (25000 MPA.S); Sodium Polyacrylate (2500000 MW); Silicon Dioxide; Ethylhexylglycerin; Shea Butter; Hyaluronic Acid; Glycerin; .Alpha.-Bisabolol, (+/-)-; Tetrasodium Glutamate Diacetate; Banana; Coconut Oil

Vacation® Face Lotion

Drug Facts

Active ingredients

Avobenzone (3%), Homosalate (10%), Octisalate (5%), Octocrylene (10%)

Purpose

Sunscreen

Uses

- Helps prevent sunburn.
- If used as directed with other sun protection measures (see Directions), decreases the risk of skin cancer and early skin aging caused by the sun.

Warnings

- For external use only.

- Do not use on damaged or broken skin.

- When using this product, keep out of eyes. Rinse with water to remove.

- Stop use and ask a doctor if rash occurs.

- Keep out of reach of children. If swallowed, get medical help or contact a Poison Control Center right away.

Directions

- Apply liberally 15 minutes before sun exposure.
- Reapply:
  - after 80 minutes of swimming or sweating
  - immediately after towel drying
  - at least every 2 hours
- Sun Protection Measures. Spending time in the sun increases your risk of skin cancer and early skin aging. To decrease the risk, regularly use a sunscreen with a broad spectrum SPF of 15 or higher and other sun protection measures, including:
  - limit time in the sun, especially from 10 a.m.-2 p.m.
  - wear long-sleeved shirts, pants, hats, and sunglasses
- Children under 6 months of age: ask a doctor.

Inactive ingredients

Water, Polymethylsilsesquioxane, Cetearyl Alcohol, Argania Spinosa (Argan) Kernel Oil, Tocopheryl Acetate (Vitamin E), Aloe Barbadensis (Aloe Vera) Leaf Juice, Niacinamide (Vitamin B3), Trimethylpentanediol/Adipic Acid/Glycerin Crosspolymer, Butyrospermum Parkii (Shea) Butter, Musa Sapientum (Banana) Fruit Extract, Cocos Nucifera (Coconut) Fruit Extract, Hyaluronic Acid, Glycerin, Bisabolol, Sodium Stearoyl Glutamate, Sodium Polyacrylate, Silica, Phenoxyethanol, Ethylhexylglycerin, Tetrasodium Glutamate Diacetate, Fragrance

Other information

Protect the product in this container from excessive heat and direct sun.

Distributed by
Vacation Inc.
936 SW 1st Ave #888
Miami, FL 33130

PRINCIPAL DISPLAY PANEL - 89 ML Bottle Label

SPF 45

FACE

SPF 45
FACE
LOTION

Vacation®

Premium Sunscreen Face Lotion
Broad Spectrum SPF 45
Water Resistant (80 Minutes)
Dermatologist Tested

3 FL OZ / 89 ML